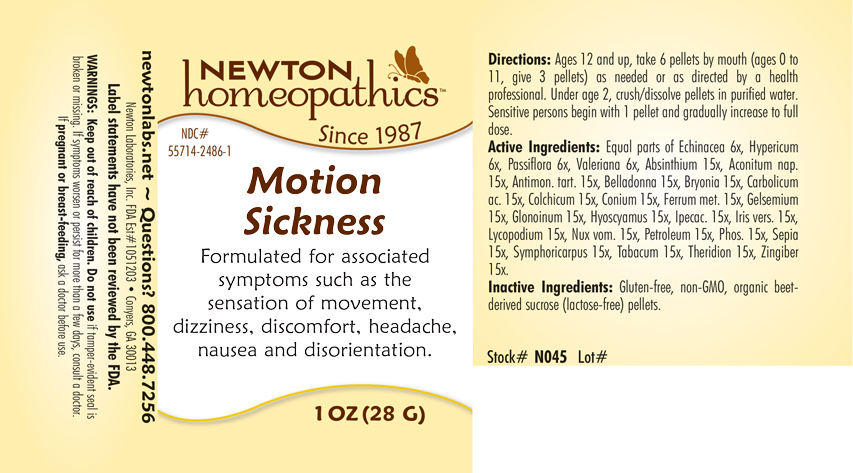 DRUG LABEL: Motion Sickness
NDC: 55714-2486 | Form: PELLET
Manufacturer: Newton Laboratories, Inc.
Category: homeopathic | Type: HUMAN OTC DRUG LABEL
Date: 20250207

ACTIVE INGREDIENTS: ECHINACEA, UNSPECIFIED 6 [hp_X]/1 g; PASSIFLORA INCARNATA FLOWERING TOP 6 [hp_X]/1 g; VALERIAN 6 [hp_X]/1 g; WORMWOOD 15 [hp_X]/1 g; THERIDION CURASSAVICUM 15 [hp_X]/1 g; ACONITUM NAPELLUS 15 [hp_X]/1 g; ANTIMONY POTASSIUM TARTRATE 15 [hp_X]/1 g; ATROPA BELLADONNA 15 [hp_X]/1 g; BRYONIA ALBA ROOT 15 [hp_X]/1 g; PHENOL 15 [hp_X]/1 g; COLCHICUM AUTUMNALE BULB 15 [hp_X]/1 g; CONIUM MACULATUM FLOWERING TOP 15 [hp_X]/1 g; IRON 15 [hp_X]/1 g; GELSEMIUM SEMPERVIRENS ROOT 15 [hp_X]/1 g; NITROGLYCERIN 15 [hp_X]/1 g; HYOSCYAMUS NIGER 15 [hp_X]/1 g; IPECAC 15 [hp_X]/1 g; IRIS VERSICOLOR ROOT 15 [hp_X]/1 g; LYCOPODIUM CLAVATUM SPORE 15 [hp_X]/1 g; STRYCHNOS NUX-VOMICA SEED 15 [hp_X]/1 g; KEROSENE 15 [hp_X]/1 g; PHOSPHORUS 15 [hp_X]/1 g; SEPIA OFFICINALIS JUICE 15 [hp_X]/1 g; SYMPHORICARPOS ALBUS FRUIT 15 [hp_X]/1 g; TOBACCO LEAF 15 [hp_X]/1 g; HYPERICUM PERFORATUM 6 [hp_X]/1 g; GINGER 15 [hp_X]/1 g
INACTIVE INGREDIENTS: SUCROSE

Motion 2486P

INDICATIONS & USAGE SECTION

Formulated for associated symptoms such as the sensation of movement, dizziness, discomfort, headache, nausea and disorientation.

DOSAGE & ADMINISTRATION SECTION

Directions: Ages 12 and up, take 6 pellets by mouth (ages 0 to 11, give 3 pellets) as needed or as directed by a health professional. Under age 2, crush/dissolve pellets in purified water. Sensitive persons begin with 1 pellet and gradually increase to full dose.

OTC - ACTIVE INGREDIENT SECTION

Equal parts of Echinacea 6x, Hypericum perforatum 6x, Passiflora incarnata 6x, Valeriana officinalis 6x, Absinthium 15x, Aconitum napellus 15x, Antimonium tartaricum 15x, Belladonna 15x, Bryonia 15x, Carbolicum acidum 15x, Colchicum autumnale 15x, Conium maculatum 15x, Ferrum metallicum 15x, Gelsemium sempervirens 15x, Glonoinum 15x, Hyoscyamus niger 15x, Ipecacuanha 15x, Iris versicolor 15x, Lycopodium clavatum 15x, Nux vomica 15x, Petroleum 15x, Phosphorus 15x, Sepia 15x, Symphoricarpus racemosus 15x, Tabacum 15x, Theridion 15x, Zingiber officinale 15x.

OTC - PURPOSE SECTION

Formulated for associated symptoms such as the sensation of movement, dizziness, discomfort, headache, nausea and disorientation.

INACTIVE INGREDIENT SECTION

Inactive Ingredients: Gluten-free, non-GMO, organic beet-derived sucros (lactose-free) pellets.

QUESTIONS SECTION

newtonlabs.net – Questions? 800.448.7256

Newton Laboratories, Inc. FDA Est # 1051203 - Conyers, GA 30013

WARNINGS SECTION

WARNINGS: Keep out of reach of children. Do not use if tamper-evident seal is broken or missing. If symptoms worsen or persist for more than a few days, consult a doctor. If pregnant or breast-feeding, ask a doctor before use.

OTC - PREGNANCY OR BREAST FEEDING SECTION

If pregnant or breast-feeding, ask a doctor before use.

OTC - KEEP OUT OF REACH OF CHILDREN SECTION

Keep out of reach of children.